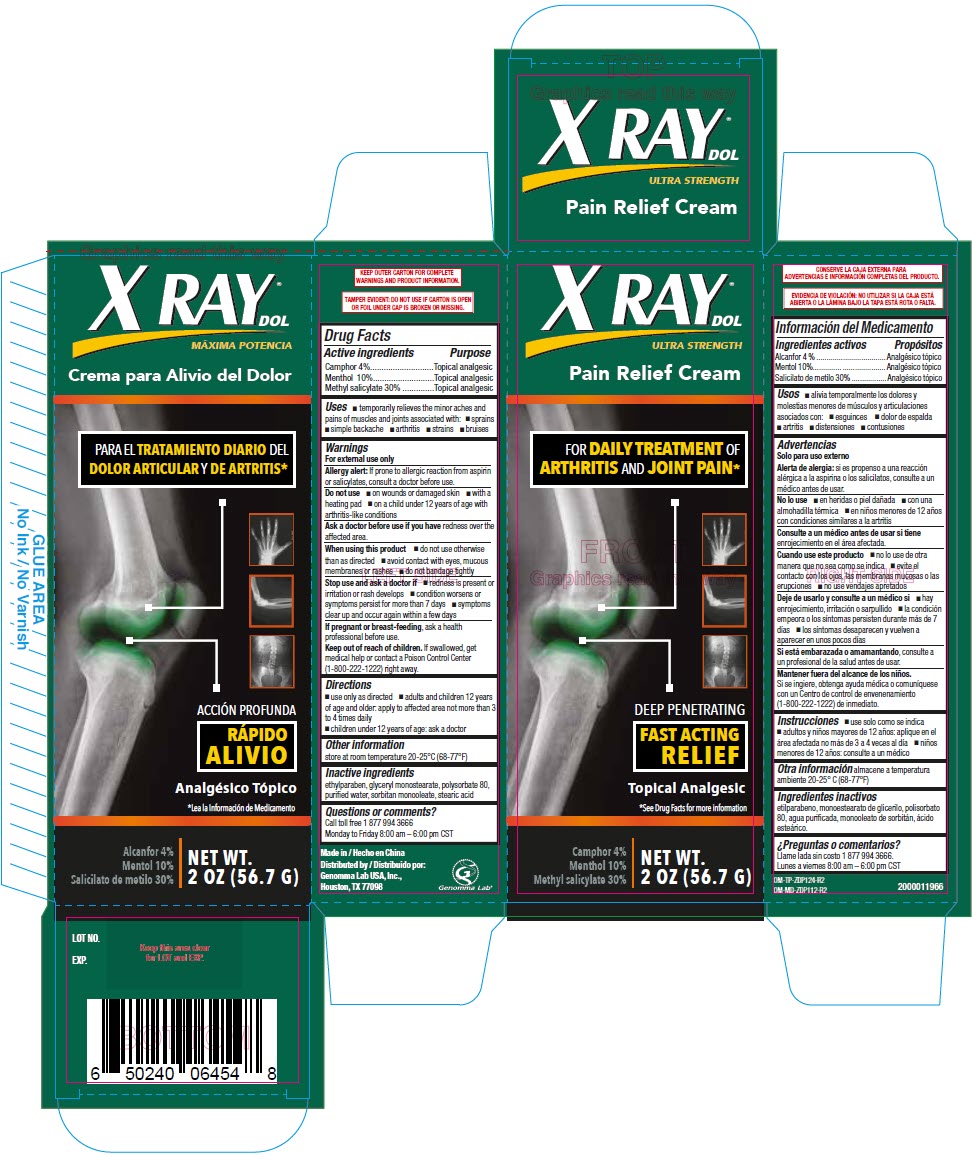 DRUG LABEL: XRay Pain Relief
NDC: 50066-456 | Form: CREAM
Manufacturer: Genomma Lab USA
Category: otc | Type: HUMAN OTC DRUG LABEL
Date: 20231227

ACTIVE INGREDIENTS: MENTHOL, (+)- 100 mg/1 g; CAMPHOR, (-)- 40 mg/1 g; METHYL SALICYLATE 300 mg/1 g
INACTIVE INGREDIENTS: glyceryl monostearate; Water; Polysorbate 80; sorbitan monooleate; stearic acid; ethylparaben

XRay® Pain Relief Cream

Drug Facts

ACTIVE INGREDIENT

Active ingredients | Purpose
Camphor 4% | Topical analgesic
Menthol 10% | Topical analgesic
Methyl salicylate 30% | Topical analgesic

Uses

- temporarily relieves the minor aches and pains of muscles and joints associated with:
  - sprains
  - simple backache
  - arthritis
  - strains
  - bruises

Warnings

For external use only

Allergy alert

If prone to allergic reaction from aspirin or salicylates, consult a doctor before use.

Do not use

- on wounds or damaged skin
- with a heating pad
- on a child under 12 years of age with arthritis-like conditions

Ask a doctor before use if you have redness over the affected area.

When using this product

- do not use otherwise than as directed
- avoid contact with eyes, mucous membranes or rashes
- do not bandage tightly

Stop use and ask a doctor if

- redness is present or irritation or rash develops
- condition worsens or symptoms persist for more than 7 days
- symptoms clear up and occur again within a few days

PREGNANCY OR BREAST FEEDING

If pregnant or breast-feeding, ask a health professional before use.

Keep out of reach of children. If swallowed, get medical help or contact a Poison Control Center (1-800-222-1222) right away.

Directions

- use only as directed
- adults and children 12 years of age and older: apply to affected area not more than 3 to 4 times daily
- children under 12 years of age: ask a doctor

Other information

store at room temperature 20-25°C (68-77°F)

Inactive ingredients

ethylparaben, glyceryl monostearate, polysorbate 80, purified water, sorbitan monooleate, stearic acid

Questions or comments?

Call toll free 1 877 994 3666

Monday to Friday 8:00 am – 6:00 pm CST

Distributed by:
Genomma Lab USA, Inc.,
Houston, TX 77098

PRINCIPAL DISPLAY PANEL - 56.7 G Tube Carton

X RAY®
DOL

ULTRA STRENGTH

Pain Relief Cream

FOR DAILY TREATMENT OF
ARTHRITIS AND JOINT PAIN*

DEEP PENETRATING

FAST ACTING
RELIEF

Topical Analgesic

*See Drug Facts for more information

Camphor 4%
Menthol 10%
Methyl salicylate 30%

NET WT.
2 OZ (56.7 G)